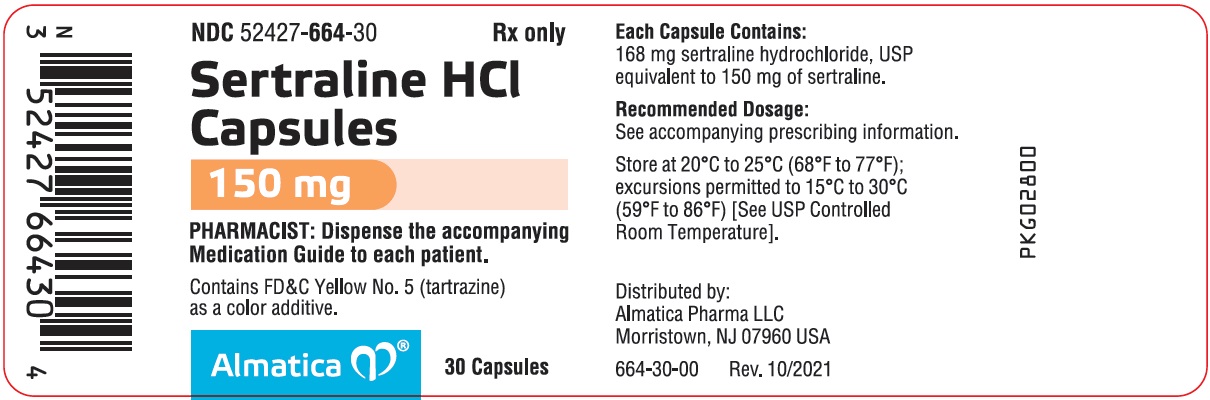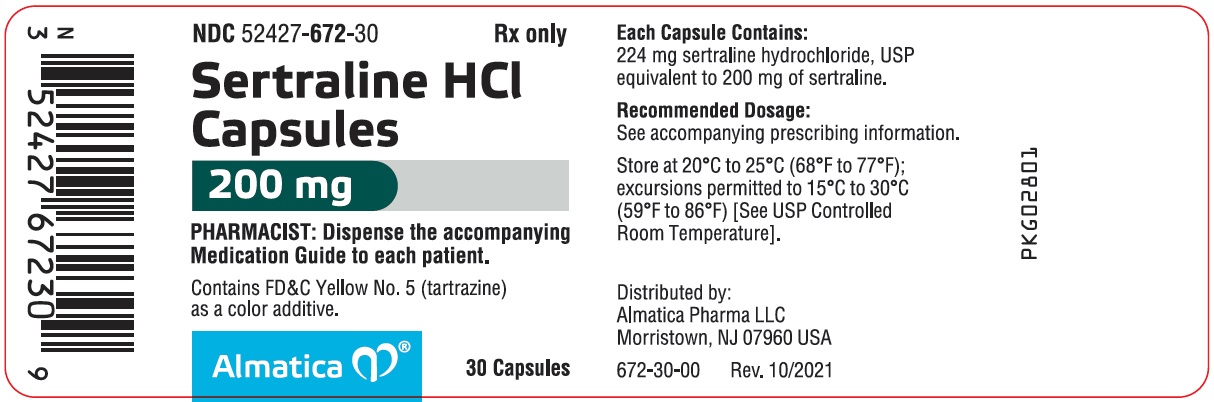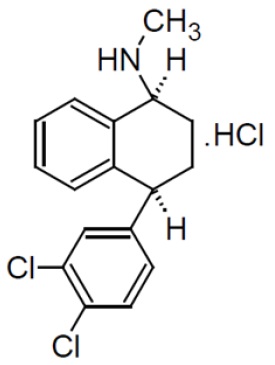 DRUG LABEL: sertraline HCl
NDC: 52427-664 | Form: CAPSULE
Manufacturer: Almatica Pharma LLC
Category: prescription | Type: HUMAN PRESCRIPTION DRUG LABEL
Date: 20230824

ACTIVE INGREDIENTS: SERTRALINE HYDROCHLORIDE 150 mg/1 1
INACTIVE INGREDIENTS: CROSCARMELLOSE SODIUM; GELATIN, UNSPECIFIED; HYDROXYPROPYL CELLULOSE, UNSPECIFIED; MAGNESIUM STEARATE; MICROCRYSTALLINE CELLULOSE; SILICON DIOXIDE; TITANIUM DIOXIDE; FD&C YELLOW NO. 5

HIGHLIGHTS OF PRESCRIBING INFORMATION

These highlights do not include all the information needed to use SERTRALINE HYDROCHLORIDE CAPSULES safely and effectively. See full prescribing information for SERTRALINE HYDROCHLORIDE CAPSULES.
SERTRALINE HYDROCHLORIDE capsules, for oral use
Initial U.S. Approval: 1991

RECENT MAJOR CHANGES

Warnings and Precautions (5.2, 5.3) | 8/2023

WARNING: SUICIDAL THOUGHTS AND BEHAVIORS

See full prescribing information for complete boxed warning.

Increased risk of suicidal thoughts and behavior in pediatric and young adult patients taking antidepressants. Closely monitor all antidepressant-treated patients for clinical worsening and emergence of suicidal thoughts and behaviors (5.1)

1 INDICATIONS AND USAGE

Sertraline Hydrochloride (HCl) Capsules is a selective serotonin reuptake inhibitor (SSRI) indicated for the treatment of (1):

- Major depressive disorder (MDD) in adults
- Obsessive-compulsive disorder (OCD) in adults and pediatric patients 6 years and older

2 DOSAGE AND ADMINISTRATION

- Do not initiate treatment with Sertraline HCl Capsules. Use another sertraline HCl product for initial dosage, titration, and dosages below 150 mg once daily (2.1)
- Recommended dosage is 150 mg or 200 mg once daily (2.1)
- Maximum recommended dosage is 200 mg once daily (2.1)
- Swallow capsules whole. Do not open, crush, or chew (2.2)
- When discontinuing Sertraline HCl Capsules, reduce dose gradually whenever possible. Gradual dosage reduction will require use of another sertraline HCl product (2.5, 5.5)

3 DOSAGE FORMS AND STRENGTHS

- Capsules: 150 mg and 200 mg (3)

4 CONTRAINDICATIONS

- Concomitant use of monoamine oxidase inhibitors (MAOIs), or use within 14 days of stopping MAOIs (4, 7.1)
- Concomitant use of pimozide (4, 7.1)
- Known hypersensitivity to sertraline or excipients (4)

5 WARNINGS AND PRECAUTIONS

- Serotonin Syndrome: Increased risk when co-administered with other serotonergic agents, but also when taken alone. If it occurs, discontinue Sertraline HCl Capsules and serotonergic agents and initiate supportive treatment (4, 5.2, 7.1)
- Increased Risk of Bleeding: Concomitant use of aspirin, nonsteroidal anti-inflammatory drugs (NSAIDs), other antiplatelet drugs, warfarin, and other anticoagulants may increase this risk (5.3)
- Activation of Mania or Hypomania: Screen patients for bipolar disorder (5.4)
- Discontinuation Syndrome: When discontinuing Sertraline HCl Capsules, reduce dosage gradually whenever possible, and monitor for discontinuation symptoms. Gradual reduction will require use of another sertraline HCl product (5.5)
- Seizures: Use with caution in patients with seizure disorders (5.6)
- Angle Closure Glaucoma: Avoid use of antidepressants, including Sertraline HCl Capsules, in patients with untreated anatomically narrow angles (5.7)
- QTc Prolongation: Sertraline HCl Capsules should be used with caution in patients with risk factors for QTc prolongation (5.10)
- Allergic Reactions to FD&C Yellow No. 5 (Tartrazine): Contains FD&C Yellow No. 5 (tartrazine) which may cause allergic-type reactions (including bronchial asthma) in certain susceptible persons (5.11)
- Sexual Dysfunction: Sertraline HCl Capsules may cause symptoms of sexual dysfunction (5.12)

6 ADVERSE REACTIONS

Most common adverse reactions (≥5% and twice placebo) in pooled placebo-controlled clinical trials with sertraline HCl were nausea, diarrhea/loose stool, tremor, dyspepsia, decreased appetite, hyperhidrosis, ejaculation failure, and decreased libido (6.1)

To report SUSPECTED ADVERSE REACTIONS, contact Almatica Pharma LLC at 1-877-447-7979 or FDA at 1-800-FDA-1088 or www.fda.gov/medwatch.

7 DRUG INTERACTIONS

- Protein-bound drugs: Monitor for adverse reactions and reduce dosage of Sertraline HCl Capsules or other protein-bound drugs (e.g., warfarin) as warranted (7.1, 12.3)
- CYP2D6 substrates: Reduce dosage of drugs metabolized by CYP2D6 (7.1, 12.3)

8 USE IN SPECIFIC POPULATIONS

- Pregnancy: Third trimester use may increase risk for persistent pulmonary hypertension and symptoms of poor adaptation (respiratory distress, temperature instability, feeding difficulty, hypotonia, irritability) in the neonate (8.1)
- Pediatric use: Safety and effectiveness in pediatric patients other than those with OCD (6 to 17 years) have not been established (8.4)
- Hepatic Impairment: Not recommended (8.6)

FULL PRESCRIBING INFORMATION

WARNING: SUICIDAL THOUGHTS AND BEHAVIORS

Antidepressants increased the risk of suicidal thoughts and behavior in pediatric and young adult patients in short-term studies. Closely monitor all antidepressant-treated patients for clinical worsening, and for emergence of suicidal thoughts and behaviors [see Warnings and Precautions (5.1)].

1 INDICATIONS AND USAGE

Sertraline Hydrochloride (HCl) Capsules is indicated for the treatment of the following [see Clinical Studies (14)]:

- Major depressive disorder (MDD) in adults
- Obsessive-compulsive disorder (OCD) in adults and pediatric patients 6 years and older

2 DOSAGE AND ADMINISTRATION

2.1 Dosage in Patients with MDD and OCD

Do not initiate treatment with Sertraline HCl Capsules because the only available dose strengths are 150 mg and 200 mg. Use another sertraline HCl product for initial dosage, titration, and dosages below 150 mg once daily. Refer to Prescribing Information of the other sertraline HCl products for the recommended dosage for those products.

Sertraline HCl Capsules can be initiated in patients receiving 100 mg or 125 mg of sertraline HCl for at least one week. The recommended dosage of Sertraline HCl Capsules is 150 mg or 200 mg once daily. The maximum recommended dosage is 200 mg once daily.

2.2 Administration Instructions

Administer Sertraline HCl Capsules orally. Swallow capsules whole; do not open, crush, or chew.

2.3 Screen for Bipolar Disorder Prior to Starting Sertraline HCl Capsules

Prior to initiating treatment with Sertraline HCl Capsules or another antidepressant, screen patients for a personal or family history of bipolar disorder, mania, or hypomania [see Warnings and Precautions (5.4)].

2.4 Switching Patients to or from a Monoamine Oxidase Inhibitor Antidepressant

At least 14 days must elapse between discontinuation of a monoamine oxidase inhibitor (MAOI) antidepressant and initiation of Sertraline HCl Capsules. In addition, at least 14 days must elapse after stopping Sertraline HCl Capsules before starting an MAOI antidepressant [see Contraindications (4), Warnings and Precautions (5.2)].

2.5 Discontinuation of Treatment with Sertraline HCl Capsules

Adverse reactions may occur upon discontinuation of Sertraline HCl Capsules [see Warnings and Precautions (5.5)]. Gradually reduce the dosage rather than stopping Sertraline HCl Capsules abruptly whenever possible. Given that dosage strengths lower than 150 mg of Sertraline HCl Capsules are not available, gradual dosage reduction will require the use of another sertraline HCl product.

3 DOSAGE FORMS AND STRENGTHS

150 mg capsules: Hard shell capsules, with "ALM" printed axially on the opaque yellow cap and "664" printed axially on the opaque white body.

200 mg capsules: Hard shell capsules, with "ALM" printed axially on the opaque yellowish green cap and "672" printed axially on the opaque white body.

Dosage strengths are based on the active moiety, sertraline. The 150 mg capsules contain 168 mg of sertraline HCl. The 200 mg capsules contain 224 mg of sertraline HCl.

4 CONTRAINDICATIONS

Sertraline HCl Capsules are contraindicated in patients:

- Taking, or within 14 days of stopping, MAOIs, (including the MAOIs linezolid and intravenous methylene blue) because of an increased risk of serotonin syndrome [see Warnings and Precautions (5.2), Drug Interactions (7.1)].
- Taking pimozide [see Drug Interactions (7.1)].
- With known hypersensitivity to sertraline or the excipients in Sertraline HCl Capsules (e.g., anaphylaxis, angioedema) [see Adverse Reactions (6.1, 6.2)].

5 WARNINGS AND PRECAUTIONS

5.1 Suicidal Thoughts and Behaviors in Adolescent and Young Adults

In pooled analyses of placebo-controlled trials of antidepressant drugs (SSRIs and other antidepressant classes) that included approximately 77,000 adult patients and over 4,500 pediatric patients, the incidence of suicidal thoughts and behaviors in antidepressant-treated patients age 24 years and younger was greater than in placebo-treated patients. There was considerable variation in risk of suicidal thoughts and behaviors among drugs, but there was an increased risk identified in young patients for most drugs studied. There were differences in absolute risk of suicidal thoughts and behaviors across the different indications, with the highest incidence in patients with MDD. The drug-placebo differences in the number of cases of suicidal thoughts and behaviors per 1,000 patients treated are provided in Table 1.

Table 1: Risk Differences of the Number of Patients of Suicidal Thoughts or Behavior in the Pooled Placebo-Controlled Trials of Antidepressants in Pediatric and Adult Patients
Age Range | Drug-Placebo Difference in Number of Patients of Suicidal Thoughts or Behaviors per 1,000 Patients Treated
Increases Compared to Placebo
<18 years old | 14 additional patients
18 to 24 years old | 5 additional patients
Decreases Compared to Placebo
25 to 64 years old | 1 fewer patient
≥65 years old | 6 fewer patients

It is unknown whether the risk of suicidal thoughts and behaviors in children, adolescents, and young adults extends to longer-term use, i.e., beyond four months. However, there is substantial evidence from placebo-controlled maintenance trials in adults with MDD that antidepressants delay the recurrence of depression and that depression itself is a risk factor for suicidal thoughts and behaviors.

Monitor all antidepressant-treated patients for any indication for clinical worsening and emergence of suicidal thoughts and behaviors, especially during the initial few months of drug therapy, and at times of dosage changes. Counsel family members or caregivers of patients to monitor for changes in behavior and to alert the healthcare provider. Consider changing the therapeutic regimen, including possibly discontinuing Sertraline HCl Capsules, in patients whose depression is persistently worse, or who are experiencing emergent suicidal thoughts or behaviors.

5.2 Serotonin Syndrome

SSRIs, including Sertraline HCl Capsules, can precipitate serotonin syndrome, a potentially life-threatening condition. The risk is increased with concomitant use of other serotonergic drugs (including triptans, tricyclic antidepressants, fentanyl, lithium, tramadol, meperidine, methadone, tryptophan, buspirone, amphetamines, and St. John’s Wort) and with drugs that impair metabolism of serotonin, i.e., MAOIs [see Contraindications (4), Drug Interactions (7.1)]. Serotonin syndrome can also occur when these drugs are used alone.

Serotonin syndrome signs and symptoms may include mental status changes (e.g., agitation, hallucinations, delirium, and coma), autonomic instability (e.g., tachycardia, labile blood pressure, dizziness, diaphoresis, flushing, hyperthermia), neuromuscular symptoms (e.g., tremor, rigidity, myoclonus, hyperreflexia, incoordination), seizures, and gastrointestinal symptoms (e.g., nausea, vomiting, diarrhea).

The concomitant use of Sertraline HCl Capsules with MAOIs is contraindicated. In addition, do not initiate Sertraline HCl Capsules in a patient being treated with MAOIs such as linezolid or intravenous methylene blue. No reports involved the administration of methylene blue by other routes (such as oral ingestion or local tissue injection). If it is necessary to initiate treatment with an MAOI such as linezolid or intravenous methylene blue in a patient taking Sertraline HCl Capsules, discontinue Sertraline HCl Capsules before initiating treatment with the MAOI [see Contraindications (4), Drug Interactions (7.1)].

Monitor all patients taking Sertraline HCl Capsules for the emergence of serotonin syndrome. Discontinue treatment with Sertraline HCl Capsules and any concomitant serotonergic agents immediately if the above symptoms occur, and initiate supportive symptomatic treatment. If concomitant use of Sertraline HCl Capsules with other serotonergic drugs is clinically warranted, inform patients of the increased risk for serotonin syndrome and monitor for symptoms.

5.3 Increased Risk of Bleeding

Drugs that interfere with serotonin reuptake inhibition, including Sertraline HCl Capsules, increase the risk of bleeding events. Concomitant use of aspirin, nonsteroidal anti-inflammatory drugs (NSAIDs), other antiplatelet drugs, warfarin, and other anticoagulants may add to this risk. Case reports and epidemiological studies (case-control and cohort design) have demonstrated an association between use of drugs that interfere with serotonin reuptake and the occurrence of gastrointestinal bleeding. Based on data from the published observational studies, exposure to SSRIs, particularly in the month before delivery, has been associated with a less than 2-fold increase in the risk of postpartum hemorrhage [see Use in Specific Populations (8.1)]. Bleeding events related to drugs that interfere with serotonin reuptake have ranged from ecchymosis, hematoma, epistaxis, and petechiae to life-threatening hemorrhages.

Inform patients about the increased risk of bleeding associated with the concomitant use of Sertraline HCl Capsules and antiplatelet agents or anticoagulants. For patients taking warfarin, carefully monitor the international normalized ratio.

5.4 Activation of Mania or Hypomania

In patients with bipolar disorder, treating a depressive episode with Sertraline HCl Capsules or another antidepressant may precipitate a mixed/manic episode. In controlled clinical trials with another sertraline HCl product, patients with bipolar disorder were generally excluded; however, symptoms of mania or hypomania were reported in 0.4% of patients treated with sertraline. Prior to initiating treatment with Sertraline HCl Capsules, screen patients for any personal or family history of bipolar disorder, mania, or hypomania [see Dosage and Administration (2.3)].

5.5 Discontinuation Syndrome

Adverse reactions after discontinuation of serotonergic antidepressants, particularly after abrupt discontinuation, include: nausea, sweating, dysphoric mood, irritability, agitation, dizziness, sensory disturbances (e.g., paresthesia, such as electric shock sensations), tremor, anxiety, confusion, headache, lethargy, emotional lability, insomnia, hypomania, tinnitus, and seizures. A gradual reduction in dosage rather than abrupt cessation is recommended whenever possible [see Dosage and Administration (2.5)].

5.6 Seizures

Sertraline HCl has not been systematically evaluated in patients with seizure disorders. Patients with a history of seizures were excluded from clinical studies. Sertraline HCl Capsules should be prescribed with caution in patients with a seizure disorder.

5.7 Angle-Closure Glaucoma

The pupillary dilation that occurs following use of many antidepressant drugs, including sertraline HCl, may trigger an angle closure attack in a patient with anatomically narrow angles who does not have a patent iridectomy. Avoid use of antidepressants, including Sertraline HCl Capsules, in patients with untreated anatomically narrow angles.

5.8 Hyponatremia

Hyponatremia may occur as a result of treatment with SSRIs, including Sertraline HCl Capsules. Cases with serum sodium lower than 110 mmol/L have been reported with another sertraline HCl product. Signs and symptoms of hyponatremia include headache, difficulty concentrating, memory impairment, confusion, weakness, and unsteadiness, which may lead to falls. Signs and symptoms associated with more severe or acute cases have included hallucination, syncope, seizure, coma, respiratory arrest, and death. In many cases, this hyponatremia appears to be the result of the syndrome of inappropriate antidiuretic hormone secretion (SIADH).

In patients with symptomatic hyponatremia, discontinue Sertraline HCl Capsules and institute appropriate medical intervention. Elderly patients, patients taking diuretics, and those who are volume-depleted may be at greater risk of developing hyponatremia with SSRIs [see Use in Specific Populations (8.5)].

5.9 False-Positive Effects on Screening Tests for Benzodiazepines

False-positive urine immunoassay screening tests for benzodiazepines have been reported in patients taking another sertraline HCl product. This finding is due to lack of specificity of the screening tests. False-positive test results may be expected for several days following discontinuation of Sertraline HCl Capsules. Confirmatory tests, such as gas chromatography/mass spectrometry, will help distinguish Sertraline HCl Capsules from benzodiazepines [see Drug Interactions (7.3)].

5.10 QTc Prolongation

During post-marketing use of sertraline, cases of QTc prolongation and Torsade de Pointes (TdP) have been reported. Most reports were confounded by other risk factors. In a randomized, double-blind, placebo- and positive-controlled three-period crossover thorough QTc study in 54 healthy adult subjects, there was a positive relationship between the length of the rate-adjusted QTc interval and serum sertraline concentration. Therefore, Sertraline HCl Capsules should be used with caution in patients with risk factors for QTc prolongation [see Drug Interactions (7.1), Clinical Pharmacology (12.2)].

5.11 Allergic Reactions to FD&C Yellow No. 5 (Tartrazine)

Sertraline HCl Capsules contain FD&C Yellow No. 5 (tartrazine), which may cause allergic-type reactions (including bronchial asthma) in certain susceptible persons. Although the overall incidence of FD&C Yellow No. 5 (tartrazine) sensitivity in the general population is low, it is frequently seen in patients who also have aspirin hypersensitivity.

5.12 Sexual Dysfunction

Use of SSRIs, including Sertraline HCl Capsules, may cause symptoms of sexual dysfunction [see Adverse Reactions (6.1)]. In male patients, SSRI use may result in ejaculatory delay or failure, decreased libido, and erectile dysfunction. In female patients, SSRI use may result in decreased libido and delayed or absent orgasm.

It is important for prescribers to inquire about sexual function prior to initiation of Sertraline HCl Capsules and to inquire specifically about changes in sexual function during treatment, because sexual function may not be spontaneously reported. When evaluating changes in sexual function, obtaining a detailed history (including timing of symptom onset) is important because sexual symptoms may have other causes, including the underlying psychiatric disorder. Discuss potential management strategies to support patients in making informed decisions about treatment.

6 ADVERSE REACTIONS

The following adverse reactions are described in more detail in other sections of the prescribing information:

- Hypersensitivity reactions to sertraline or excipients of Sertraline HCl Capsules [see Contraindications (4)]
- Suicidal Thoughts and Behaviors in Adolescent and Young Adults [see Warnings and Precautions (5.1)]
- Serotonin Syndrome [see Contraindications (4), Warnings and Precautions (5.2), Drug Interactions (7.1)]
- Increased Risk of Bleeding [see Warnings and Precautions (5.3)]
- Activation of Mania or Hypomania [see Warnings and Precautions (5.4)]
- Discontinuation Syndrome [see Warnings and Precautions (5.5)]
- Seizures [see Warnings and Precautions (5.6)]
- Angle-Closure Glaucoma [see Warnings and Precautions (5.7)]
- Hyponatremia [see Warnings and Precautions (5.8)]
- QTc Prolongation [see Warnings and Precautions (5.10)]
- Allergic reactions to FD&C Yellow No. 5 (Tartrazine) [see Warnings and Precautions (5.11)]
- Sexual Dysfunction [see Warnings and Precautions (5.12)]

6.1 Clinical Trials Experience

Because clinical trials are conducted under widely varying conditions, adverse reaction rates observed in the clinical trials of a drug cannot be directly compared to rates in the clinical trials of another drug and may not reflect the rates observed in practice.

The safety of Sertraline HCl Capsules for the treatment of MDD and OCD is based on adequate and well-controlled studies of another sertraline HCl product. Below is a display of adverse reactions of sertraline HCl (referred to as “sertraline” in this section) from those adequate and well-controlled studies in MDD, OCD, and other conditions.

The data described below reflect exposure in randomized, double-blind, placebo-controlled trials of sertraline in 3066 adults. These 3066 patients exposed to sertraline for 8 to 12 weeks represent 568 patient-years of exposure. The mean age was 40 years; 57% were females and 43% were males.

The most common adverse reactions (≥5% and twice placebo) in all pooled placebo-controlled clinical trials of all sertraline-treated patients (MDD, OCD, and other conditions) were nausea, diarrhea/loose stool, tremor, dyspepsia, decreased appetite, hyperhidrosis, ejaculation failure, and decreased libido (see Table 2). The following are the most common adverse reactions in trials of sertraline (≥5% and twice placebo) by indication that were not mentioned previously.

- MDD: somnolence
- OCD: insomnia, agitation

Table 2: Common Adverse Reactions (Greater than 2% of Adults with MDD, OCD, and Other Conditions Treated with Sertraline Hydrochloride and Greater than or Equal to Twice the Incidence of Placebo) in Pooled Placebo-Controlled Trials*
 | Sertraline Hydrochloride (N=3066) % | Placebo (N=2293) %
Cardiac disorders
Palpitations | 4 | 2
Eye disorders
Visual impairment | 4 | 2
Gastrointestinal Disorders
Nausea | 26 | 12
Diarrhea/Loose Stools | 20 | 10
Dry mouth | 14 | 9
Dyspepsia | 8 | 4
Constipation | 6 | 4
Vomiting | 4 | 1
General disorders and administration site conditions
Fatigue | 12 | 8
Metabolism and nutrition disorders
Decreased appetite | 7 | 2
Nervous system disorders
Dizziness | 12 | 8
Somnolence | 11 | 6
Tremor | 9 | 2
Psychiatric Disorders
Insomnia | 20 | 13
Agitation | 8 | 5
Libido Decreased | 6 | 2
Reproductive system and breast disorders
Ejaculation failure (1) | 8 | 1
Erectile dysfunction (1) | 4 | 1
Ejaculation disorder (1) | 3 | 0
Male sexual dysfunction (1) | 2 | 0
Skin and subcutaneous tissue disorders
Hyperhidrosis | 7 | 3
(1) Denominator used was for male patients only (n=1316 sertraline; n=973 placebo).
* Adverse reactions that occurred greater than 2% in sertraline hydrochloride-treated patients and at least 2% greater in sertraline hydrochloride-treated patients than placebo-treated patients.

Adverse Reactions Leading to Discontinuation in Placebo-Controlled Clinical Trials

In all placebo-controlled studies, 368 (12%) of the 3066 patients who received sertraline discontinued treatment due to an adverse reaction, compared with 93 (4%) of the 2293 placebo-treated patients. In placebo-controlled studies, the following were the common adverse reactions leading to discontinuation in sertraline-treated patients:

- All sertraline -treated patients (MDD, OCD, and Other Conditions): nausea (3%), diarrhea (2%), agitation (2%), and insomnia (2%).
- MDD (>2% and twice placebo): decreased appetite, dizziness, fatigue, headache, somnolence, tremor, and vomiting.
- OCD: somnolence.

Male and Female Sexual Dysfunction

Although changes in sexual desire, sexual performance and sexual satisfaction often occur as manifestations of a psychiatric disorder, they may also be a consequence of SSRI treatment. However, reliable estimates of the incidence and severity of untoward experiences involving sexual desire, performance and satisfaction are difficult to obtain, in part because patients and healthcare providers may be reluctant to discuss them. Accordingly, estimates of the incidence of untoward sexual experience and performance cited in labeling may underestimate their actual incidence.

Table 3 below displays the incidence of sexual adverse reactions reported by at least 2% of sertraline -treated patients and twice placebo from pooled placebo-controlled trials of MDD, OCD, and other conditions. For men and all indications, the most common adverse reactions (>2% and twice placebo) included: ejaculation failure, decreased libido, erectile dysfunction, ejaculation disorder, and male sexual dysfunction. For women, the most common adverse reaction (≥2% and twice placebo) was decreased libido.

Table 3: Most Common Sexual Adverse Reactions (≥2% and twice placebo) in Men or Women from Sertraline Hydrochloride Pooled Controlled Trials in Adults with MDD, OCD, and Other Conditions
 | Sertraline Hydrochloride % | Placebo %
Men only | (N=1316) | (N=973)
Ejaculation failure | 8 | 1
Libido decreased | 7 | 2
Erectile dysfunction | 4 | 1
Ejaculation disorder | 3 | 0
Male sexual dysfunction | 2 | 0
Women only | (N=1750) | (N=1320)
Libido decreased | 4 | 2

Adverse Reactions in Pediatric Patients

In 281 pediatric patients treated with sertraline in placebo-controlled studies, the overall profile of adverse reactions was generally similar to that seen in adult studies. Adverse reactions that do not appear in Table 2 (most common adverse reactions in adults) yet were reported in at least 2% of pediatric patients and at a rate of at least twice the placebo rate include fever, hyperkinesia, urinary incontinence, aggression, epistaxis, purpura, arthralgia, decreased weight, muscle twitching, and anxiety.

Other Adverse Reactions Observed During the Premarketing Evaluation of Sertraline

Other infrequent adverse reactions, not described elsewhere in the prescribing information, occurring at an incidence of < 2% in patients treated with sertraline were:

Cardiac disorders – tachycardia

Ear and labyrinth disorders – tinnitus

Endocrine disorders - hypothyroidism

Eye disorders - mydriasis, blurred vision

Gastrointestinal disorders - hematochezia, melena, rectal hemorrhage

General disorders and administration site conditions - edema, gait disturbance, irritability, pyrexia

Hepatobiliary disorders - elevated liver enzymes

Immune system disorders - anaphylaxis

Metabolism and nutrition disorders - diabetes mellitus, hypercholesterolemia, hypoglycemia, increased appetite

Musculoskeletal and connective tissue disorders – arthralgia, muscle spasms, tightness, or twitching

Nervous system disorders - ataxia, coma, convulsion, decreased alertness, hypoesthesia, lethargy, psychomotor hyperactivity, syncope

Psychiatric disorders - aggression, bruxism, confusional state, euphoric mood, hallucination

Renal and urinary disorders - hematuria

Reproductive system and breast disorders - galactorrhea, priapism, vaginal hemorrhage

Respiratory, thoracic and mediastinal disorders - bronchospasm, epistaxis, yawning

Skin and subcutaneous tissue disorders - alopecia; cold sweat; dermatitis; dermatitis bullous; pruritus; purpura; erythematous, follicular, or maculopapular rash; urticaria

Vascular disorders - hemorrhage, hypertension, vasodilation

6.2 Postmarketing Experience

The following adverse reactions have been identified during post-approval use of another sertraline product. Because these reactions are reported voluntarily from a population of uncertain size, it is not always possible to reliably estimate their frequency or establish a causal relationship to drug exposure.

Bleeding or clotting disorders - increased coagulation times (altered platelet function)

Cardiac disorders - AV block, bradycardia, atrial arrhythmias, QTc-interval prolongation, ventricular tachycardia (including Torsade de Pointes) [see Clinical Pharmacology (12.2)]

Endocrine disorders - gynecomastia, hyperprolactinemia, menstrual irregularities, SIADH

Eye disorders - blindness, optic neuritis, cataract

Hepatobiliary disorders - severe liver events (including hepatitis, jaundice, liver failure with some fatal outcomes), pancreatitis

Hemic and lymphatic disorders - agranulocytosis, aplastic anemia and pancytopenia, leukopenia, thrombocytopenia, lupus-like syndrome, serum sickness

Immune system disorders - angioedema

Metabolism and nutrition disorders - hyponatremia, hyperglycemia

Musculoskeletal and connective tissue disorders - rhabdomyolysis, trismus

Nervous system disorders - serotonin syndrome, extrapyramidal symptoms (including akathisia and dystonia), oculogyric crisis

Psychiatric disorders - psychosis, enuresis, paroniria

Renal and urinary disorders - acute renal failure

Respiratory, thoracic and mediastinal disorders - pulmonary hypertension, anosmia, hyposmia

Skin and subcutaneous tissue disorders - photosensitivity skin reaction and other severe cutaneous reactions, which potentially can be fatal, such as Stevens-Johnson Syndrome (SJS) and toxic epidermal necrolysis (TEN)

Vascular disorders - cerebrovascular spasm (including reversible cerebral vasoconstriction syndrome and Call-Fleming syndrome), vasculitis

7 DRUG INTERACTIONS

7.1 Clinically Significant Drug Interactions

Table 4 includes clinically significant drug interactions with Sertraline HCl Capsules [see Clinical Pharmacology (12.3)].

Table 4. Clinically-Significant Drug Interactions with Sertraline HCl Capsules
Monoamine Oxidase Inhibitors (MAOIs)
Clinical Impact: | The concomitant use of SSRIs, including Sertraline HCl Capsules, and MAOIs increases the risk of serotonin syndrome.
Intervention: | Sertraline HCl Capsules is contraindicated in patients taking MAOIs, including MAOIs such as linezolid or intravenous methylene blue [see Dosage and Administration (2.4), Contraindications (4), Warnings and Precautions (5.2)].
Pimozide
Clinical Impact: | Increased plasma concentrations of pimozide, a drug with a narrow therapeutic index, may increase the risk of QTc prolongation and ventricular arrhythmias.
Intervention: | Concomitant use of pimozide and Sertraline HCl Capsules is contraindicated [see Contraindications (4)].
Other Serotonergic Drugs
Clinical Impact: | Concomitant use of Sertraline HCl Capsules with other serotonergic drugs (including other SSRIs, SNRIs, triptans, tricyclic antidepressants, opioids, lithium, buspirone, amphetamines, tryptophan, and St. John's Wort) increases the risk of serotonin syndrome.
Intervention: | Monitor patients for signs and symptoms of serotonin syndrome, particularly during treatment initiation and dosage increases. If serotonin syndrome occurs, consider discontinuation of Sertraline HCl Capsules and/or concomitant serotonergic drugs [see Warnings and Precautions (5.2)].
Drugs that Interfere with Hemostasis (antiplatelet agents and anticoagulants)
Clinical Impact: | The concurrent use of an antiplatelet agent or anticoagulant with Sertraline HCl Capsules may potentiate the risk of bleeding.
Intervention: | Inform patients of the increased risk of bleeding associated with the concomitant use of Sertraline HCl Capsules and antiplatelet agents and anticoagulants. For patients taking warfarin, carefully monitor the international normalized ratio [see Warnings and Precautions (5.3)].
Drugs Highly Bound to Plasma Protein
Clinical Impact: | Sertraline is highly bound to plasma protein. The concomitant use of Sertraline HCl Capsules with another drug that is highly bound to plasma protein may increase free concentrations of sertraline or other tightly-bound drugs in plasma [see Clinical Pharmacology (12.3)].
Intervention: | Monitor for adverse reactions and reduce dosage of Sertraline HCl Capsules or other protein-bound drugs as warranted.
Drugs Metabolized by CYP2D6
Clinical Impact: | Sertraline HCl Capsules are a CYP2D6 inhibitor [see Clinical Pharmacology (12.3)]. The concomitant use of Sertraline HCl Capsules with a CYP2D6 substrate may increase the exposure of the CYP2D6 substrate.
Intervention: | Decrease the dosage of a CYP2D6 substrate if needed with concomitant Sertraline HCl Capsules use. Conversely, an increase in dosage of a CYP2D6 substrate may be needed if Sertraline HCl Capsules are discontinued.
Phenytoin
Clinical Impact: | Phenytoin is a narrow therapeutic index drug. Sertraline HCl Capsules may increase phenytoin concentrations.
Intervention: | Monitor phenytoin levels when initiating or titrating Sertraline HCl Capsules. Reduce phenytoin dosage if needed.
Drugs that Prolong the QTc Interval
Clinical Impact: | The risk of QTc prolongation and/or ventricular arrhythmias (e.g., TdP) is increased with concomitant use of Sertraline HCl Capsules with other drugs which prolong the QTc interval [see Warnings and Precautions (5.10), Clinical Pharmacology (12.2)].
Intervention: | Pimozide is contraindicated for use with Sertraline HCl Capsules. Avoid the concomitant use of drugs known to prolong the QTc interval.

7.2 Drugs Having No Clinically Important Interactions with Sertraline HCl

Based on pharmacokinetic studies with another sertraline HCl formulation, no dosage adjustment of Sertraline HCl Capsules is necessary when used in combination with cimetidine. Additionally, no dosage adjustment is required for diazepam, lithium, atenolol, tolbutamide, digoxin, and drugs metabolized by CYP3A4, when Sertraline HCl Capsules is administered concomitantly [see Clinical Pharmacology (12.3)].

7.3 False-Positive Screening Tests for Benzodiazepines

False-positive urine immunoassay screening tests for benzodiazepines have been reported in patients taking another sertraline HCl product. This finding is due to lack of specificity of the screening tests. False-positive test results may be expected for several days following discontinuation of Sertraline HCl Capsules. Confirmatory tests, such as gas chromatography/mass spectrometry, will distinguish sertraline from benzodiazepines.

8 USE IN SPECIFIC POPULATIONS

8.1 Pregnancy

Pregnancy Exposure Registry

There is a pregnancy exposure registry that monitors pregnancy outcomes in women exposed to antidepressants during pregnancy. Healthcare providers should encourage patients to enroll by calling the National Pregnancy Registry for Antidepressants at 1-866-961-2388 or visiting online at https://womensmentalhealth.org/research/pregnancyregistry/antidepressants.

Risk Summary

Based on data from published observational studies, exposure to SSRIs, particularly in the month before delivery, has been associated with a less than 2-fold increase in the risk of postpartum hemorrhage [see Warnings and Precautions (5.3) and Clinical Considerations].

Overall, available published epidemiologic studies of pregnant women exposed to sertraline in the first trimester suggest no difference in major birth defect risk compared to the background rate for major birth defects in comparator populations. Some studies have reported increases for specific major birth defects; however, these study results are inconclusive (see Data). There are clinical considerations regarding neonates exposed to SSRIs, including Sertraline HCl Capsules, during the third trimester of pregnancy (see Clinical Considerations).

Although no malformations were observed in animal reproduction studies, delayed fetal ossification was observed when sertraline was administered during the period of organogenesis at doses less than the maximum recommended human dose (MRHD) in rats and doses approximately 4 times the MRHD in rabbits on a mg/m^2 basis in adults. When sertraline was administered to female rats during the last third of gestation, there was an increase in the number of stillborn pups and pup deaths during the first four days after birth at the MRHD (see Data).

The background risk of major birth defects and miscarriage for the indicated population are unknown. In the U.S. general population, the estimated background risk of major birth defects and miscarriage in clinically recognized pregnancies is 2 to 4% and 15 to 20%, respectively. Advise a pregnant woman of possible risks to the fetus when prescribing Sertraline HCl Capsules.

Clinical Considerations

Disease-Associated Maternal and/or Embryo/Fetal Risk

A prospective longitudinal study followed 201 pregnant women with a history of major depression who were euthymic taking antidepressants at the beginning of pregnancy. The women who discontinued antidepressants during pregnancy were more likely to experience a relapse of major depression than women who continued antidepressants. Consider the risks of untreated depression when discontinuing or changing treatment with antidepressant medication during pregnancy and postpartum.

Maternal Adverse Reactions

Use of Sertraline HCl Capsules in the month before delivery may be associated with an increased risk of postpartum hemorrhage [see Warnings and Precautions (5.3)].

Fetal/Neonatal Adverse Reactions

Exposure to SSRIs, including Sertraline HCl Capsules, in late pregnancy may lead to an increased risk for neonatal complications requiring prolonged hospitalization, respiratory support, and tube feeding, and/or persistent pulmonary hypertension of the newborn (PPHN).

When treating a pregnant woman with Sertraline HCl Capsules during the third trimester, carefully consider both the potential risks and benefits of treatment. Monitor neonates who were exposed to sertraline in the third trimester of pregnancy for PPHN and drug discontinuation syndrome (see Data).

Data

Human Data

Third Trimester Exposure

Neonates exposed to sertraline and other SSRIs late in the third trimester have developed complications requiring prolonged hospitalization, respiratory support, and tube feeding. These findings are based on post-marketing reports. Such complications can arise immediately upon delivery. Reported clinical findings have included respiratory distress, cyanosis, apnea, seizures, temperature instability, feeding difficulty, vomiting, hypoglycemia, hypotonia, hypertonia, hyperreflexia, tremor, jitteriness, irritability, and constant crying. These features are consistent with either a direct toxic effect of SSRIs or, possibly, a drug discontinuation syndrome. In some cases, the clinical picture was consistent with serotonin syndrome [see Warnings and Precautions (5.2)].

Exposure during late pregnancy to SSRIs may have an increased risk for persistent pulmonary hypertension of the newborn (PPHN). PPHN occurs in 1 to 2 per 1,000 live births in the general population and is associated with substantial neonatal morbidity and mortality. In a retrospective case-control study of 377 women whose infants were born with PPHN and 836 women whose infants were born healthy, the risk for developing PPHN was approximately six-fold higher for infants exposed to SSRIs after the 20th week of gestation compared to infants who had not been exposed to antidepressants during pregnancy. A study of 831,324 infants born in Sweden in 1997 to 2005 found a PPHN risk ratio of 2.4 (95% CI 1.2 to 4.3) associated with patient-reported maternal use of SSRIs “in early pregnancy” and a PPHN risk ratio of 3.6 (95% CI 1.2 to 8.3) associated with a combination of patient-reported maternal use of SSRIs “in early pregnancy” and an antenatal SSRI prescription “in later pregnancy”.

First Trimester Exposure

The weight of evidence from epidemiologic studies of pregnant women exposed to sertraline in the first trimester suggest no difference in major birth defect risk compared to the background rate for major birth defects in pregnant women who were not exposed to sertraline. A meta-analysis of studies suggest no increase in the risk of total malformations (summary odds ratio=1.01, 95% CI=0.88 to 1.17) or cardiac malformations (summary odds ratio=0.93, 95% CI=0.70 to 1.23) among offspring of women with first trimester exposure to sertraline. An increased risk of congenital cardiac defects, specifically septal defects, the most common type of congenital heart defect, was observed in some published epidemiologic studies with first trimester sertraline exposure; however, most of these studies were limited by the use of comparison populations that did not allow for the control of confounders such as the underlying depression and associated conditions and behaviors, which may be factors associated with increased risk of these malformations.

Animal Data

Reproduction studies have been performed in rats and rabbits at doses up to 80 mg/kg/day and 40 mg/kg/day, respectively. These doses correspond to approximately 4 times the maximum recommended human dose (MRHD) of 200 mg/day on a mg/m^2 basis in adults. There was no evidence of malformation at any dose level. When pregnant rats and rabbits were given sertraline during the period of organogenesis, delayed ossification was observed in fetuses at doses of 10 mg/kg (0.5 times the MRHD on a mg/m^2 basis) in rats and 40 mg/kg (3.9 times the MRHD on a mg/m^2 basis) in rabbits. When female rats received sertraline during the last third of gestation and throughout lactation, there was an increase in stillborn pups and pup deaths during the first 4 days after birth. Pup body weights were also decreased during the first four days after birth. These effects occurred at a dose of 20 mg/kg (1 times the MRHD on a mg/m^2 basis). The no effect dose for rat pup mortality was 10 mg/kg (0.5 times the MRHD on a mg/m^2 basis). The decrease in pup survival was shown to be due to in utero exposure to sertraline. The clinical significance of these effects is unknown.

8.2 Lactation

Risk Summary

Available data from published literature demonstrate low levels of sertraline and its metabolites in human milk (see Data). There are no data on the effects of sertraline on milk production. The developmental and health benefits of breastfeeding should be considered along with the mother’s clinical need for Sertraline HCl Capsules and any potential adverse effects on the breastfed infant from the drug or from the underlying maternal condition.

Data

In a published pooled analysis of 53 mother-infant pairs, exclusively human milk-fed infants had an average of 2% (range 0% to 15%) of the sertraline serum levels measured in their mothers. No adverse reactions were observed in these infants.

8.4 Pediatric Use

The safety and effectiveness of Sertraline HCl Capsules have been established in the treatment of OCD in pediatric patients aged 6 to 17 [see Adverse Reactions (6.1), Clinical Pharmacology (12.3), Clinical Studies (14.2)]. Safety and effectiveness in pediatric patients with OCD below the age of 6 have not been established.

Safety and effectiveness have not been established in pediatric patients for indications other than OCD. Two placebo-controlled trials were conducted with another sertraline HCl product in pediatric patients with MDD, but the data were not sufficient to support an indication for use in pediatric patients.

Monitoring Pediatric Patients Treated with Sertraline HCl Capsules

Monitor all patients being treated with antidepressants for clinical worsening, suicidal thoughts, and unusual changes in behavior, especially during the initial few months of treatment, or at times of dose increases or decreases [see Boxed Warning, Warnings and Precautions (5.1)]. Decreased appetite and weight loss have been observed with the use of SSRIs. Monitor weight and growth in pediatric patients treated with SSRIs including Sertraline HCl Capsules.

Weight Loss in Studies in Pediatric Patients with MDD

In a pooled analysis of two 10-week, double-blind, placebo-controlled, flexible dose (50 to 200 mg) outpatient trials for MDD (n=373) with another sertraline HCl product, there was a difference in weight change between sertraline HCl and placebo of roughly 1 kg, for both pediatric patients ages 6 to 11 and pediatric patients ages 12 to 17, in both age groups representing a slight weight loss for the sertraline HCl group compared to a slight gain for the placebo group. For pediatric patients (ages 6 to 11), about 7% of the sertraline HCl-treated patients had a weight loss greater than 7% of body weight compared to 0% of the placebo-treated patients; for pediatric patients (ages 12 to 17), about 2% of sertraline HCl-treated patients had a weight loss > 7% of body weight compared to about 1% of placebo-treated patients.

A subset of patients who completed the randomized controlled trials in patients with MDD (sertraline n=99, placebo n=122) were continued into a 24-week, flexible-dose, open-label, extension study. Those subjects who completed 34 weeks of sertraline HCl treatment (10 weeks in a placebo-controlled trial + 24 weeks open-label, n=68) had weight gain that was similar to that expected using data from age-adjusted peers. However, there are no studies that directly evaluate the long-term effects of sertraline HCl on the growth, development, and maturation in pediatric patients.

Juvenile Animal Toxicity Data

A study conducted in juvenile rats at clinically relevant doses showed delay in sexual maturation, but there was no effect on fertility in either males or females.

In this study in which juvenile rats were treated with oral doses of sertraline at 0, 10, 40 or 80 mg/kg/day from postnatal day 21 to 56, a delay in sexual maturation was observed in males treated with 80 mg/kg/day and females treated with doses ≥10 mg/kg/day. There was no effect on male and female reproductive endpoints or neurobehavioral development up to the highest dose tested (80 mg/kg/day), except a decrease in auditory startle response in females at 40 and 80 mg/kg/day at the end of treatment but not at the end of the drug-free period. The highest dose of 80 mg/kg/day produced plasma levels (AUC) of sertraline 5 times those seen in pediatric patients (6 to 17 years of age) receiving the maximum recommended dose of sertraline (200 mg/day).

8.5 Geriatric Use

Of the total number of patients with MDD, OCD, and other conditions in clinical studies with another sertraline product, 797 (17%) were ≥ 65 years old, while 197 (4%) were ≥ 75 years old.

No overall differences in safety or effectiveness were observed between these subjects and younger subjects, and other reported clinical experience has not identified differences in responses between the elderly and younger patients. In general, dose selection for an elderly patient should be conservative, usually starting at the low end of the dosing range, reflecting the greater frequency of decreased hepatic, renal, or cardiac function, and of concomitant disease or other drug therapy.

In 354 geriatric subjects treated with another sertraline HCl product in MDD placebo-controlled trials, the overall profile of adverse reactions was generally similar to that shown in Table 2 [see Adverse Reactions (6.1)], except for tinnitus, arthralgia with an incidence of at least 2% and at a rate greater than placebo in geriatric patients.

SSRIs, including sertraline HCl, have been associated with cases of clinically significant hyponatremia in elderly patients, who may be at greater risk for this adverse reaction [see Warnings and Precautions (5.8)].

8.6 Hepatic Impairment

Sertraline HCl Capsules are not recommended in patients with mild (Child-Pugh score 5 or 6), moderate (Child-Pugh score 7 to 10), or severe (Child-Pugh score 10 to 15) hepatic impairment. The effect of Sertraline HCl Capsules in patients with mild, moderate, or severe hepatic impairment was not studied.

Sertraline plasma exposure was higher in patients with mild hepatic impairment, compared with those with normal hepatic function [see Clinical Pharmacology (12.3)].

Dosage adjustments are not possible with the available strengths of Sertraline HCl Capsules.

8.7 Renal Impairment

No dose adjustment is necessary in patients with mild (eGFR 60 to 89 mL/minute/1.73 m^2), moderate (eGFR 30 to 59 mL/minute/1.73 m^2), or severe renal impairment (eGFR 15 to 29 mL/minute/1.73 m^2). Sertraline exposure does not appear to be affected by renal impairment [see Clinical Pharmacology (12.3)].

9 DRUG ABUSE AND DEPENDENCE

9.1 Controlled Substance

Sertraline HCl Capsules contain sertraline, which is not a controlled substance.

9.2 Abuse

In a placebo-controlled, double-blind, randomized study of the comparative abuse liability of another sertraline HCl product, alprazolam, and d-amphetamine in humans, sertraline HCl did not produce the positive subjective effects indicative of abuse potential, such as euphoria or drug liking, that were observed with the other two drugs.

10 OVERDOSAGE

The following have been reported with sertraline HCl tablet overdosage:

- Seizures, which may be delayed, and altered mental status including coma.
- Cardiovascular toxicity, which may be delayed, including QRS and QTc interval prolongation. Hypertension most commonly seen, but rarely can see hypotension alone or with co-ingestants including alcohol.
- Serotonin syndrome (patients with a multiple drug overdosage with other proserotonergic drugs may have a higher risk).

Gastrointestinal decontamination with activated charcoal should be considered in patients who present early after a sertraline overdose. Consider contacting a Poison Center (1-800-221-2222) or a medical toxicologist for additional overdosage management recommendations.

11 DESCRIPTION

Sertraline HCl Capsules contain sertraline HCl, a selective serotonin reuptake inhibitor (SSRI). Sertraline HCl has a molecular weight of 342.7 and has the following chemical name: (1S,4S)-4-(3,4-dichlorophenyl)-N-methyl-tetralin-1-amine hydrochloride. The empirical formula C17H17Cl2N • HCl is represented by the following structural formula:

Sertraline HCl is a white to almost white crystalline powder that is slightly soluble in water, acetone and isopropyl alcohol.

Sertraline HCl Capsules is for oral administration and contain 168 mg and 224 mg sertraline HCl, equivalent to 150 mg and 200 mg sertraline, and the following inactive ingredients: croscarmellose sodium, gelatin, hydroxypropyl cellulose, magnesium stearate, microcrystalline cellulose, silicon dioxide and titanium dioxide. The 150 mg capsules contain FD&C Yellow No. 5 as a color additive. The 200 mg capsules contain FD&C Blue No. 1 and FD&C Yellow No. 5 as color additives.

12 CLINICAL PHARMACOLOGY

12.1 Mechanism of Action

Sertraline potentiates serotonergic activity in the central nervous system through inhibition of neuronal reuptake of serotonin (5-HT).

12.2 Pharmacodynamics

Studies at clinically relevant doses have demonstrated that sertraline blocks the uptake of serotonin into human platelets. In vitro studies in animals also suggest that sertraline is a potent and selective inhibitor of neuronal serotonin reuptake and has only very weak effects on norepinephrine and dopamine neuronal reuptake. In vitro studies have shown that sertraline has no significant affinity for adrenergic (alpha1, alpha2, beta), cholinergic, GABA, dopaminergic, histaminergic, serotonergic (5HT1A, 5HT1B, 5HT2), or benzodiazepine receptors. The chronic administration of sertraline was found in animals to down regulate brain norepinephrine receptors. Sertraline does not inhibit monoamine oxidase.

Alcohol

In healthy subjects, the acute cognitive and psychomotor effects of alcohol were not potentiated by sertraline.

Cardiac Electrophysiology

The effect of sertraline on the QTc interval was evaluated in a randomized, double-blind, placebo- and positive-controlled three-period crossover thorough QTc study in 54 healthy adult subjects. At 2-fold the maximum recommended daily dose (~3-fold the steady-state exposure for sertraline and N-desmethylsertraline), the largest mean ΔΔQTc was 10 ms with upper bound of two-sided 90% confidence interval of 12 ms. The length of the QTc interval was also positively correlated with serum concentrations of sertraline and N-desmethylsertraline concentrations. These concentration-based analyses, however, indicated a lesser effect on QTc at maximally observed concentration than in the primary analysis [see Warnings and Precautions (5.10), Adverse Reactions (6), Drug Interactions (7.1), Overdosage (10)].

12.3 Pharmacokinetics

Absorption

Following a single dose of Sertraline HCl Capsule at 150 mg, the mean peak plasma concentrations (Cmax) of sertraline occurred between 4.5 to 8.4 hours post-dosing.

The average terminal elimination half-life of plasma sertraline is about 26 hours. Consistent with the terminal elimination half-life, there is an approximately two-fold accumulation up to steady-state concentrations, which are achieved after one week of once-daily dosing. Linear dose-proportional pharmacokinetics are likely over a range of 150 to 200 mg.

Effect of Food

Administration of Sertraline HCl Capsules with food causes a small increase in Cmax and AUC.

Distribution

In vitro protein binding studies performed with radiolabeled 3H-sertraline showed that sertraline is highly bound to serum proteins (98%) in the range of 20 to 500 ng/mL. However, at up to 300 and 200 ng/mL concentrations, respectively, sertraline and N-desmethylsertraline did not alter the plasma protein binding of two other highly protein bound drugs, warfarin and propranolol.

Elimination

Metabolism

Sertraline undergoes extensive first pass metabolism. The principal initial pathway of metabolism for sertraline is N-demethylation. N-desmethylsertraline has a plasma terminal elimination half-life of 62 to 104 hours. Both in vitro biochemical and in vivo pharmacological testing have shown N-desmethylsertraline to be substantially less active than sertraline.

Excretion

Both sertraline and N-desmethylsertraline undergo oxidative deamination and subsequent reduction, hydroxylation, and glucuronide conjugation. In a study of radiolabeled sertraline involving two healthy male subjects, sertraline accounted for less than 5% of the plasma radioactivity. About 40 to 45% of the administered radioactivity was recovered in urine in 9 days. Unchanged sertraline was not detectable in the urine. For the same period, about 40 to 45% of the administered radioactivity was accounted for in feces, including 12 to 14% unchanged sertraline.

Desmethylsertraline exhibits time-related, dose dependent increases in AUC (0 to 24-hour), Cmax and Cmin, with about a 5- to 9-fold increase in these pharmacokinetic parameters between day 1 and day 14.

Specific Populations

Pediatric Patients

Sertraline pharmacokinetics were evaluated in a group of 61 pediatric patients (29 aged 6 to 12 years, 32 aged 13 to 17 years) including both males (N=28) and females (N=33). Relative to the adults, pediatric patients aged 6 to 12 years and 13 to 17 years showed about 22% lower AUC (0-24 hr) and Cmax values when plasma concentration was adjusted for weight. The half-life was similar to that in adults, and no gender-associated differences were observed [see Dosage and Administration (2.1), Use in Specific Populations (8.4)].

Geriatric Patients

Sertraline plasma clearance in a group of 16 (8 male, 8 female) elderly patients treated with 100 mg/day of another sertraline HCl product for 14 days was approximately 40% lower than in a similarly studied group of younger (25 to 32 year old) individuals. Steady-state, therefore, was achieved after 2 to 3 weeks in older patients. The same study showed a decreased clearance of desmethylsertraline in older males, but not in older females [see Use in Specific Populations (8.5)].

Patients with Hepatic Impairment

In patients with chronic mild liver impairment (N=10: 8 patients with Child-Pugh scores of 5-6; and 2 patients with Child-Pugh scores of 7-8) who received 50 mg of another sertraline HCl product per day for 21 days, sertraline clearance was reduced, resulting in approximately 3-fold greater exposure compared to age-matched volunteers with normal hepatic function (N=10). The exposure to desmethylsertraline was approximately 2-fold greater in patients with mild hepatic impairment compared to age-matched volunteers with normal hepatic function. There were no significant differences in plasma protein binding observed between the two groups. The effects of sertraline in patients with moderate and severe hepatic impairment have not been studied [see Use in Specific Populations (8.6)].

Patients with Renal Impairment

Sertraline is extensively metabolized and excretion of unchanged drug in urine is a minor route of elimination. In volunteers with mild to moderate (CLcr=30-60 mL/min), moderate to severe (CLcr=10-29 mL/min) or severe (receiving hemodialysis) renal impairment (N=10 each group), the pharmacokinetics and protein binding of 200 mg sertraline per day maintained for 21 days were not altered compared to age-matched volunteers (N=12) with no renal impairment. Thus, sertraline multiple dose pharmacokinetics appear to be unaffected by renal impairment [see Use in Specific Populations (8.7)].

Drug Interaction Studies

Pimozide

In a controlled study of a single dose (2 mg) of pimozide, 200 mg of another sertraline HCl product (once daily) co-administration to steady state was associated with a mean increase in pimozide AUC and Cmax of about 40%, but was not associated with any changes in ECG. The highest recommended pimozide dose (10 mg) has not been evaluated in combination with sertraline. The effect on QTc interval and PK parameters at doses higher than 2 mg of pimozide are not known [see Drug Interactions (7.1)].

Drugs Metabolized by CYP2D6

Many antidepressant drugs (e.g., SSRIs, including sertraline, and most tricyclic antidepressant drugs) inhibit the biochemical activity of the drug metabolizing isozyme CYP2D6 (debrisoquin hydroxylase), and, thus, may increase the plasma concentrations of co-administered drugs that are metabolized by CYP2D6. The drugs for which this potential interaction is of greatest concern are those metabolized primarily by CYP2D6 and that have a narrow therapeutic index (e.g., tricyclic antidepressant drugs and the Type 1C antiarrhythmics propafenone and flecainide). The extent to which this interaction is an important clinical problem depends on the extent of the inhibition of CYP2D6 by the antidepressant and the therapeutic index of the co-administered drug. There is variability among the drugs effective in the treatment of MDD in the extent of clinically important 2D6 inhibition, and in fact sertraline at lower doses has a less prominent inhibitory effect on 2D6 than some others in the class. Nevertheless, even sertraline has the potential for clinically important 2D6 inhibition [see Drug Interactions (7.1)].

Phenytoin

Clinical trial data suggested that sertraline may increase phenytoin concentrations [see Drug Interactions (7.1)].

Cimetidine

In a study assessing disposition of sertraline (100 mg) on the second of 8 days of cimetidine administration (800 mg daily), there were increases in sertraline mean AUC (50%), Cmax (24%) and half-life (26%) compared to the placebo group [see Drug Interactions (7.2)].

Diazepam

In a study comparing the disposition of intravenously administered diazepam before and after 21 days of dosing with either sertraline (50 to 200 mg/day escalating dose) or placebo, there was a 32% decrease relative to baseline in diazepam clearance for the sertraline group compared to a 19% decrease relative to baseline for the placebo group (p<0.03). There was a 23% increase in Tmax for desmethyldiazepam in the sertraline group compared to a 20% decrease in the placebo group (p<0.03) [see Drug Interactions (7.2)].

Lithium

In a placebo-controlled trial in normal volunteers, the administration of two doses of another sertraline HCl product did not significantly alter steady-state lithium levels or the renal clearance of lithium [see Drug Interactions (7.2)].

Tolbutamide

In a placebo-controlled trial in normal volunteers, administration of another sertraline HCl product for 22 days (including 200 mg/day for the final 13 days) caused a statistically significant 16% decrease from baseline in the clearance of tolbutamide following an intravenous 1000 mg dose. Sertraline administration did not noticeably change either the plasma protein binding or the apparent volume of distribution of tolbutamide, suggesting that the decreased clearance was due to a change in the metabolism of the drug [see Drug Interactions (7.2)].

Atenolol

Sertraline (100 mg) when administered to 10 healthy male subjects had no effect on the beta-adrenergic blocking ability of atenolol [see Drug Interactions (7.2)].

Digoxin

In a placebo-controlled trial in normal volunteers, administration of another sertraline HCl product for 17 days (including 200 mg/day for the last 10 days) did not change serum digoxin levels or digoxin renal clearance [see Drug Interactions (7.2)].

Drugs Metabolized by CYP3A4

In three separate in vivo interaction studies, sertraline was co-administered with CYP3A4 substrates, terfenadine, carbamazepine, or cisapride under steady-state conditions. The results of these studies indicated that sertraline did not increase plasma concentrations of terfenadine, carbamazepine, or cisapride. These data indicate that sertraline’s extent of inhibition of CYP3A4 activity is not likely to be of clinical significance. Results of the interaction study with cisapride indicate that sertraline 200 mg (once daily) induces the metabolism of cisapride (cisapride AUC and Cmax were reduced by about 35%) [see Drug Interactions (7.2)].

Microsomal Enzyme Induction

Preclinical studies have shown sertraline to induce hepatic microsomal enzymes. In clinical studies, sertraline was shown to induce hepatic enzymes minimally as determined by a small (5%) but statistically significant decrease in antipyrine half-life following administration of 200 mg of sertraline per day for 21 days. This small change in antipyrine half-life reflects a clinically insignificant change in hepatic metabolism.

13 NONCLINICAL TOXICOLOGY

13.1 Carcinogenesis, Mutagenesis, Impairment of Fertility

Carcinogenesis

Lifetime carcinogenicity studies were carried out in CD-1 mice and Long-Evans rats at doses up to 40 mg/kg/day. These doses correspond to 1 times (mice) and 2 times (rats) the maximum recommended human dose (MRHD) of 200 mg/day on a mg/m^2 basis. There was a dose-related increase of liver adenomas in male mice receiving sertraline at 10 to 40 mg/kg (0.25 to 1.0 times the MRHD on a mg/m^2 basis). No increase was seen in female mice or in rats of either sex receiving the same treatments, nor was there an increase in hepatocellular carcinomas. Liver adenomas have a variable rate of spontaneous occurrence in the CD-1 mouse and are of unknown significance to humans. There was an increase in follicular adenomas of the thyroid in female rats receiving sertraline at 40 mg/kg (2 times the MRHD on a mg/m^2 basis); this was not accompanied by thyroid hyperplasia. While there was an increase in uterine adenocarcinomas in rats receiving sertraline at 10 to 40 mg/kg (0.5 to 2.0 times the MRHD on a mg/m^2 basis) compared to placebo controls, this effect was not clearly drug related.

Mutagenesis

Sertraline had no genotoxic effects, with or without metabolic activation, based on the following assays: bacterial mutation assay; mouse lymphoma mutation assay; and tests for cytogenetic aberrations in vivo in mouse bone marrow and in vitro in human lymphocytes.

Impairment of Fertility

A decrease in fertility was seen in one of two rat studies at a dose of 80 mg/kg (approximately 4 times the maximum recommended human dose on a mg/m^2 basis in adults).

14 CLINICAL STUDIES

14.1 Major Depressive Disorder

The efficacy of Sertraline HCl Capsules for the treatment of major depressive disorder (MDD) in adult patients is based upon adequate and well-controlled studies of another sertraline HCl product (referred to as “sertraline” in this section). The results of these adequate and well-controlled studies of sertraline are presented below.

The efficacy of sertraline as a treatment for MDD was established in two randomized, double-blind, placebo-controlled studies and one double-blind, randomized-withdrawal study following an open label study in adult (ages 18 to 65) outpatients who met the Diagnostic and Statistical Manual of Mental Disorders (DSM-III) criteria for MDD (studies MDD-1 and MDD-2).

- Study MDD-1 was an 8-week, 3-arm study with flexible dosing of sertraline, amitriptyline, and placebo. Adult patients received sertraline (N=126, in a daily dose titrated weekly to 50 mg, 100 mg, or 200 mg), amitriptyline (N=123, in a daily dose titrated weekly to 50 mg, 100 mg, or 150 mg), or placebo (N= 130).
- Study MDD-2 was a 6-week, multicenter parallel study of three fixed doses of sertraline administered once daily at 50 mg (N=82), 100 mg (N=75), and 200 mg (N=56) doses and placebo (N=76) in the treatment of adult outpatients with MDD.

Overall, these studies demonstrated sertraline to be superior to placebo on the Hamilton Rating Scale for Depression (HAMD-17) and the Clinical Global Impression Severity (CGI-S) of Illness and Global Improvement (CGI-I) scores. Study MDD-2 was not readily interpretable regarding a dose response relationship for effectiveness.

A third study (Study MDD-3) involved adult outpatients meeting the DSM-III criteria for MDD who had responded by the end of an initial 8-week open treatment phase on sertraline 50 to 200 mg/day. These patients (n=295) were randomized to continuation on double-blind sertraline 50 to 200 mg/day or placebo for 44 weeks. A statistically significantly lower relapse rate was observed for patients taking sertraline compared to those on placebo: sertraline [n=11 (8%)] and placebo [n=31 (39%)]. The mean sertraline dose for completers was 70 mg/day.

Analyses for gender effects on outcome did not suggest any differential responsiveness on the basis of sex.

14.2 Obsessive-Compulsive Disorder

The efficacy of Sertraline HCl Capsules for the treatment of OCD in adults and pediatric patients ages 6 to 17 years is based upon adequate and well-controlled studies of another sertraline HCl product (referred to as “sertraline” in this section). The results of these adequate and well-controlled studies of sertraline are presented below.

Adults with OCD

The effectiveness of sertraline in the treatment of OCD was demonstrated in three multicenter placebo-controlled studies of adult (age 18 to 65) non-depressed outpatients (Studies OCD-1, OCD-2, and OCD-3). Patients in all three studies had moderate to severe OCD (DSM-III or DSM-III-R) with mean baseline ratings on the Yale-Brown Obsessive-Compulsive Scale (Y-BOCS) total score ranging from 23 to 25.

- Study OCD-1 was an 8-week randomized, placebo-controlled study with flexible dosing of sertraline in a range of 50 to 200 mg/day, titrated in 50 mg increments every 4 days to a maximally tolerated dose; the mean dose for completers was 186 mg/day. Patients receiving sertraline (N=43) experienced a mean reduction of approximately 4 points on the Y-BOCS total score which was statistically significantly greater than the mean reduction of 2 points in placebo-treated patients (N=44). The mean change in Y-BOCS from baseline to last visit (the primary efficacy endpoint) was -3.79 (sertraline) and -1.48 (placebo).
- Study OCD-2 was a 12-week randomized, placebo-controlled fixed-dose study, including sertraline doses of 50, 100, and 200 mg/day. Sertraline (N=240) was titrated to the assigned dose over two weeks in 50 mg increments every 4 days. Patients receiving sertraline doses of 50 and 200 mg/day experienced mean reductions of approximately 6 points on the Y-BOCS total score, which were statistically significantly greater than the approximately 3 point reduction in placebo-treated patients (N=84). The mean change in Y-BOCS from baseline to last visit (the primary efficacy endpoint) was -5.7 (pooled results from sertraline 50 mg, 100 mg, and 150 mg) and -2.85 (placebo).
- Study OCD-3 was a 12-week randomized, placebo controlled study with flexible dosing of sertraline in a range of 50 to 200 mg/day; the mean dose for completers was 185 mg/day. Sertraline (N=241) was titrated to the assigned dose over two weeks in 50 mg increments every 4 days. Patients receiving sertraline experienced a mean reduction of approximately 7 points on the Y-BOCS total score which was statistically significantly greater than the mean reduction of approximately 4 points in placebo-treated patients (N=84). The mean change in Y-BOCS from baseline to last visit (the primary efficacy endpoint) was - 6.5 (sertraline) and -3.6 (placebo).

Analyses for age and gender effects on outcome did not suggest any differential responsiveness on the basis of age or sex.

The effectiveness of sertraline was studied in the risk reduction of OCD relapse. In Study OCD-4, patients ranging in age from 18 to 79 meeting DSM-III-R criteria for OCD who had responded during a 52-week single-blind trial on sertraline 50 to 200 mg/day (n=224) were randomized to continuation of sertraline or to substitution of placebo for up to 28 weeks of observation for analysis of discontinuation due to relapse or insufficient clinical response. Response during the single-blind phase was defined as a decrease in the Y-BOCS score of ≥ 25% compared to baseline and a CGI-I of 1 (very much improved), 2 (much improved) or 3 (minimally improved). Insufficient clinical response during the double-blind phase indicated a worsening of the patient’s condition that resulted in study discontinuation, as assessed by the investigator. Relapse during the double-blind phase was defined as the following conditions being met (on three consecutive visits for 1 and 2, and condition 3 being met at visit 3):

- Condition 1: Y-BOCS score increased by ≥ 5 points, to a minimum of 20, relative to baseline;
- Condition 2: CGI-I increased by ≥ one point; and
- Condition 3: Worsening of the patient’s condition in the investigator’s judgment, to justify alternative treatment.

Patients receiving continued sertraline treatment experienced a statistically significantly lower rate of discontinuation due to relapse or insufficient clinical response over the subsequent 28 weeks compared to those receiving placebo. This pattern was demonstrated in male and female subjects.

Pediatric Patients (ages 6 to 17 years) with OCD

The effectiveness of sertraline for the treatment of OCD was demonstrated in a 12-week, multicenter, placebo-controlled, parallel group study in a pediatric outpatient population (ages 6 to 17) (Study OCD-5). Sertraline (N=92) was initiated at doses of either 25 mg/day (pediatric patients ages 6 to 12) or 50 mg/day (pediatric patients ages 13 to 17), and then titrated at 3 and 4 day intervals (25 mg incremental dose for pediatric patients ages 6 to 12) or 1 week intervals (50 mg incremental dose for pediatric patients ages 13 to 17) over the next four weeks to a maximum dose of 200 mg/day, as tolerated. The mean dose for completers was 178 mg/day. Dosing was once a day in the morning or evening. Patients in this study had moderate to severe OCD (DSM-III-R) with mean baseline ratings on the Children’s Yale-Brown Obsessive-Compulsive Scale (CY-BOCS) total score of 22. Patients receiving sertraline experienced a mean reduction of approximately 7 units on the CY-BOCS total score which was statistically significantly greater than the 3 unit reduction for placebo patients (n=95). Analyses for age and gender effects on outcome did not suggest any differential responsiveness on the basis of age or sex.

16 HOW SUPPLIED/STORAGE AND HANDLING

Sertraline HCl Capsules are supplied as:

150 mg Capsules: Hard shell capsules, with "ALM" printed axially on the opaque yellow cap and "664" printed axially on the opaque white body.

NDC 52427-664-30 Bottles of 30

200 mg Capsules: Hard shell capsules, with "ALM" printed axially on the opaque yellowish green cap and "672" printed axially on the opaque white body.

NDC 52427-672-30 Bottles of 30

Store at 20°C to 25°C (68°F to 77°F); excursions permitted to 15°C to 30°C (59°F to 86°F) [See USP Controlled Room Temperature].

17 PATIENT COUNSELING INFORMATION

Advise the patient to read the FDA-approved patient labeling (Medication Guide).

Suicidal Thoughts and Behaviors

Advise patients and caregivers to look for the emergence of suicidality, especially early during treatment and when the dosage is adjusted up or down, and instruct them to report such symptoms to the healthcare provider [see Boxed Warning and Warnings and Precautions (5.1)].

Serotonin Syndrome

Caution patients about the risk of serotonin syndrome, particularly with the concomitant use of Sertraline HCl Capsules with other serotonergic drugs including triptans, tricyclic antidepressants, opioids, lithium, tryptophan, buspirone, amphetamines, St. John’s Wort, and with drugs that impair metabolism of serotonin (in particular, MAOIs, both those intended to treat psychiatric disorders and also others, such as linezolid). Instruct patients to contact their health care provider or report to the emergency room if they experience signs or symptoms of serotonin syndrome [see Warnings and Precautions (5.2), Drug Interactions (7.1)].

Increased Risk of Bleeding

Inform patients about the concomitant use of Sertraline HCl Capsules with aspirin, NSAIDs, other antiplatelet drugs, warfarin, or other anticoagulants because the combined use has been associated with an increased risk of bleeding. Advise patients to inform their health care providers if they are taking or planning to take any prescription or over-the-counter medications that increase the risk of bleeding [see Warnings and Precautions (5.3)].

Activation of Mania or Hypomania

Advise patients and their caregivers to observe for signs of activation of mania/hypomania and instruct them to report such symptoms to the healthcare provider [see Warnings and Precautions (5.4)].

Discontinuation Syndrome

Advise patients not to abruptly discontinue Sertraline HCl Capsules and to discuss any tapering regimen with their healthcare provider. Inform patients that adverse reactions can occur when Sertraline HCl Capsules is discontinued [see Warnings and Precautions (5.5)].

Sexual Dysfunction

Advise patients that use of Sertraline HCl Capsules may cause symptoms of sexual dysfunction in both male and female patients. Inform patients that they should discuss any changes in sexual function and potential management strategies with their healthcare provider [see Warnings and Precautions (5.12)].

Allergic Reactions and Reactions to FD&C Yellow No. 5 (Tartrazine)

Advise patients to notify their healthcare provider if they develop an allergic reaction such as rash, hives, swelling, or difficulty breathing [see Adverse Reactions (6.2)].

Advise patients that Sertraline HCl Capsules contain FD&C Yellow No. 5 (tartrazine), which may cause allergic-type reactions (including bronchial asthma) in certain susceptible persons or in patients who also have an aspirin hypersensitivity [see Warnings and Precautions (5.11)].

Pregnancy

Advise women to notify their healthcare provider if they are pregnant or are planning to become pregnant during treatment with Sertraline HCl Capsules. Advise women that there is a pregnancy exposure registry that monitors pregnancy outcomes of women exposed to Sertraline HCl Capsules during pregnancy.

Inform women that Sertraline HCl Capsules may cause withdrawal symptoms in the newborn or persistent pulmonary hypertension of the newborn (PPHN) [see Use in Specific Populations (8.1)].

Distributed by:
Almatica Pharma LLC
Morristown, NJ 07960 USA

PI664-01

MEDICATION GUIDE
Sertraline (ser' tra leen) HCl
capsules

What is the most important information I should know about Sertraline Hydrochloride (HCl) Capsules?
Sertraline HCl Capsules may cause serious side effects, including:

- Increased risk of suicidal thoughts or actions.
- Sertraline HCl Capsules and other antidepressant medicines may increase suicidal thoughts or actions in some people 24 years of age and younger, especially within the first few months of treatment or when the dose is changed.
  How can I watch for and try to prevent suicidal thoughts and actions?
  - Depression or other mental illnesses are the most important causes of suicidal thoughts or actions.
  - Pay close attention to any changes, especially sudden changes in mood, behavior, thoughts or feelings or if you or your child develop suicidal thoughts or actions. This is very important when an antidepressant medicine is started or when the dose is changed.
  - Call your healthcare provider right away to report new or sudden changes in mood, behavior, thoughts or feelings or if you or your child develop suicidal thoughts or actions.
  - Keep all follow-up visits with your healthcare provider and call between visits if you are worried about symptoms.
  Call your healthcare provider or get emergency help right away if you or your child have any of the following symptoms, especially if they are new, worse, or worry you:
  - attempts to commit suicide
  - acting aggressive or violent
  - new or worse depression
  - feeling agitated, restless, angry, or irritable
  - an increase in activity and talking more than what is normal for you
  - acting on dangerous impulses
  - thoughts about suicide or dying
  - new or worse anxiety or panic attacks
  - trouble sleeping
  - other unusual changes in behavior or mood

What are Sertraline HCl Capsules?
Sertraline HCl Capsules are a prescription medicine used to treat:

- A certain type of depression called Major Depressive Disorder (MDD) in adults.
- Obsessive Compulsive Disorder (OCD) in adults and children 6 years and older.
- It is not known if Sertraline HCl Capsules are safe and effective for use in children under 6 years of age with OCD or children with other behavioral health conditions.

Do not take Sertraline HCl Capsules if you or your child:

- are taking, or have stopped taking within the last 14 days, a monoamine oxidase inhibitor (MAOI).
- are being treated with the antibiotic linezolid or intravenous methylene blue.
- are taking the antipsychotic medicine pimozide because this can cause serious problems.
- are allergic to sertraline or any of the ingredients in Sertraline HCl Capsules. See the end of this Medication Guide for a complete list of ingredients in Sertraline HCl Capsules.

Ask your healthcare provider or pharmacist if you are not sure if you or your child take an MAOI or one of these medicines, including the antibiotic linezolid or intravenous methylene blue.
Do not start taking an MAOI for at least 14 days after you or your child have stopped treatment with Sertraline HCl Capsules.

Before taking Sertraline HCl Capsules, tell your healthcare provider about all medical conditions, including if you or your child:

- have or have had bleeding problems
- have, or have a family history of, bipolar disorder, mania, or hypomania
- have or have had seizures or convulsions
- have high pressure in the eye (glaucoma)
- have low sodium levels in your blood
- have heart problems
- have kidney or liver problems
- have an allergy or sensitivity to FD&C Yellow No. 5 (Tartrazine)
- are pregnant or plan to become pregnant. Sertraline HCl Capsules may harm the unborn baby. Taking Sertraline HCl Capsules during the third trimester of pregnancy may cause the baby to have withdrawal symptoms after birth or may cause the baby to be at an increased risk for a serious lung problem at birth. Talk to your healthcare provider about the risk to the mother and the unborn baby if Sertraline HCl Capsules are taken during pregnancy.
  - Tell your healthcare provider right away if you or your child becomes pregnant during treatment with Sertraline HCl Capsules.
  - There is a pregnancy registry for females who are exposed to Sertraline HCl Capsules during pregnancy. The purpose of the registry is to collect information about the health of females exposed to Sertraline HCl Capsules and their baby. If you or your child become pregnant during treatment with Sertraline HCl Capsules, talk to your healthcare provider about registering with the National Pregnancy Registry for Antidepressants. You can register by calling 1-866-961-2388 or by visiting online at https://womensmentalhealth.org/research/pregnancyregistry/antidepressants/.
- are breastfeeding or plan to breastfeed. Sertraline HCl Capsules may pass into breast milk. Talk to your healthcare provider about the best way to feed the baby during treatment with Sertraline HCl Capsules.

Tell your healthcare provider about all the medicines that you or your child take, including prescription and over-the-counter medicines, vitamins, and herbal supplements.
Sertraline HCl Capsules and some medicines may interact with each other causing serious side effects. Sertraline HCl Capsules may affect the way other medicines work and other medicines may affect the way Sertraline HCl Capsules works. Sometimes the doses of other medicines will need to be changed during treatment with Sertraline HCl Capsules. Your healthcare provider will decide whether Sertraline HCl Capsules can be taken with other medicines.
Especially tell your healthcare provider if you or your child take:

- medicines used to treat migraine headaches called triptans
- tricyclic antidepressants
- lithium
- tramadol, fentanyl, meperidine, methadone, or other opioids
- tryptophan
- buspirone
- amphetamines
- phenytoin
- St. John’s Wort
- medicines that can affect blood clotting such as aspirin, nonsteroidal anti-inflammatory drugs (NSAIDs), other antiplatelet medicines, warfarin, and other anticoagulants
- diuretics

Ask your healthcare provider if you are not sure if you or your child take any of these medicines. Your healthcare provider or pharmacist can tell you if it is safe to take Sertraline HCl Capsules with other medicines.
Do not start or stop any other medicines during treatment with Sertraline HCl Capsules without talking to your healthcare provider first. Stopping Sertraline HCl Capsules suddenly may cause you or your child to have serious side effects. See, “What are the possible side effects of Sertraline HCl Capsules?”
Know the medicines you or your child take. Keep a list of them to show to your healthcare provider and pharmacist when you get a new medicine.

How should I take Sertraline HCl Capsules?

- Take Sertraline HCl Capsules exactly as prescribed. Your healthcare provider may need to change the dose of Sertraline HCl Capsules until it is the right dose.
- Take Sertraline HCl Capsules with or without food.
- Swallow Sertraline HCl Capsules whole. Do not open, crush, or chew Sertraline HCl Capsules.
- If you miss a dose of Sertraline HCl Capsules, take the missed dose as soon as you remember. If it is almost time for the next dose, skip the missed dose and take the next dose at the regular time. Do not take 2 doses of Sertraline HCl Capsules at the same time.
- In case of overdose, get medical help or contact a live Poison Control expert right away at 1-800-222-1222. Advice is also available online at poisonhelp.org.

What are the possible side effects of Sertraline HCl Capsules?
Sertraline HCl Capsules may cause serious side effects, including:

- See, "What is the most important information I should know about Sertraline HCl Capsules?"
- Serotonin Syndrome. A potentially life-threatening problem called serotonin syndrome can happen when Sertraline HCl Capsules are taken with certain other medicines. See, “Who should not take Sertraline HCl Capsules?” Call your healthcare provider or go to the nearest hospital emergency room right away if you or your child have any of the following signs and symptoms of serotonin syndrome:
  - agitation
  - seeing or hearing things that are not real (hallucinations)
  - confusion
  - coma
  - fast heartbeat
  - changes in blood pressure
  - dizziness
  - sweating
  - flushing
  - high body temperature (hyperthermia)
  - shaking (tremors), stiff muscles, or muscle twitching
  - loss of coordination
  - seizures
  - nausea, vomiting, diarrhea
- Increased chance of bleeding. Taking Sertraline HCl Capsules with aspirin, NSAIDs, or blood thinners may add to this risk. Tell your healthcare provider about any unusual bleeding or bruising.
- Manic episodes. Manic episodes may happen in people with bipolar disorder who take Sertraline HCl Capsules. Symptoms may include:
  - greatly increased energy
  - unusually grand ideas
  - reckless behavior
  - talking more or faster than usual
  - racing thoughts
  - severe problems sleeping
  - excessive happiness or irritability
- Discontinuation syndrome. Suddenly stopping Sertraline HCl Capsules may cause you or your child to have serious side effects. Your healthcare provider may want to decrease the Sertraline HCl Capsules dose slowly. Symptoms may include:
  - nausea
  - sweating
  - changes in mood
  - irritability and agitation
  - dizziness
  - electric shock feeling (paresthesia)
  - tremor
  - anxiety
  - confusion
  - headache
  - tiredness
  - problems sleeping
  - hypomania
  - ringing in the ears (tinnitus)
  - seizures
- Seizures or convulsions.
- Eye problems (angle-closure glaucoma). Sertraline HCl Capsules may cause a type of eye problem called angle-closure glaucoma in people with certain eye problems. You or your child may want to undergo an eye examination to see if you or your child are at risk and receive preventative treatment if you are. Call your healthcare provider if you or your child have eye pain, changes in vision, or swelling or redness in or around the eye.
- Low sodium levels in your blood (hyponatremia). Low sodium levels in the blood that may be serious and may cause death, can happen during treatment with Sertraline HCl Capsules. Elderly people and people who take certain medicines may be at a greater risk for developing low sodium levels in the blood. Stop taking Sertraline HCl Capsules and call your healthcare provider or get emergency medical help right away if you have any signs or symptoms of hyponatremia. Signs and symptoms may include:
  - headache
  - difficulty concentrating
  - memory changes
  - confusion
  - weakness and unsteadiness which can lead to falls
  In more severe or more sudden cases, signs and symptoms include:
  - seeing or hearing things that are not real (hallucinations)
  - fainting
  - seizures
  - coma
  - stopping breathing (respiratory arrest)
- Changes in the electrical activity of the heart. Changes in the electrical activity of the heart including QTc prolongation and Torsade de Pointes (TdP) have happened in people who take sertraline which is the medicine contained in Sertraline HCl Capsules.
- FD&C Yellow No. 5. Sertraline HCl Capsules contains FD&C Yellow No. 5 (tartrazine) which may cause allergic-type reactions (including bronchial asthma) in certain people, especially people who also have an allergy to aspirin.
- Sexual problems (dysfunction). Taking selective serotonin reuptake inhibitors (SSRIs), including Sertraline HCl Capsules, may cause sexual problems.
  - Symptoms in males may include:
    - Delayed ejaculation or inability to have an ejaculation
    - Decreased sex drive
    - Problems getting or keeping an erection
  - Symptoms in females may include:
    - Decreased sex drive
    - Delayed orgasm or inability to have an orgasm
  Talk to your healthcare provider if you develop any changes in your sexual function or if you have any questions or concerns about sexual problems during treatment with Sertraline HCl Capsules. There may be treatments your healthcare provider can suggest.

The most common side effects of Sertraline HCl Capsules include:

- nausea, diarrhea, or loose stool
- tremor or shaking
- indigestion
- decreased appetite
- increased sweating
- sexual problems including decreased libido and ejaculation problems

These are not all the possible side effects of Sertraline HCl Capsules.
Call your doctor for medical advice about side effects. You may report side effects to FDA at 1-800-FDA-1088.

How should I store Sertraline HCl Capsules?

- Store Sertraline HCl Capsules at room temperature between 68°F to 77°F (20°C to 25°C).
- Keep Sertraline HCl Capsules bottle tightly closed.

Keep Sertraline HCl Capsules and all medicines out of the reach of children.

General information about the safe and effective use of Sertraline HCl Capsules.
Medicines are sometimes prescribed for purposes other than those listed in a Medication Guide. Do not use Sertraline HCl Capsules for a condition for which it was not prescribed. Do not give Sertraline HCl Capsules to other people, even if they have the same symptoms that you have. It may harm them. You may ask your healthcare provider or pharmacist for information about Sertraline HCl Capsules that is written for healthcare professionals.

What are the ingredients in Sertraline HCl Capsules?
Active ingredient: sertraline hydrochloride
Inactive ingredients: croscarmellose sodium, gelatin, hydroxypropyl cellulose, magnesium stearate, microcrystalline cellulose, silicon dioxide and titanium dioxide. The 150 mg capsules contain FD&C Yellow No. 5 as a color additive. The 200 mg capsules contain FD&C Blue No. 1 and FD&C Yellow No. 5 as color additives.
Distributed by:
Almatica Pharma LLC
Morristown, NJ 07960 USA
For more information about Sertraline Hydrochloride Capsules call Almatica Pharma LLC at 1-877-447-7979.

This Medication Guide has been approved by the U.S. Food and Drug Administration.

Revised: 8/2023
MG664-01

PACKAGE LABEL-PRINCIPAL DISPLAY PANEL - 150 mg

NDC 52427-664-30

Sertraline HCl Capsules

150 mg

PHARMACIST: Dispense the accompanying Medication Guide to each patient.

Contains FD&C Yellow No. 5 (tartrazine) as a color additive.

PACKAGE LABEL-PRINCIPAL DISPLAY PANEL - 200 mg

NDC 52427-672-30

Sertraline HCl Capsules

200 mg

PHARMACIST: Dispense the accompanying Medication Guide to each patient.

Contains FD&C Yellow No. 5 (tartrazine) as a color additive.